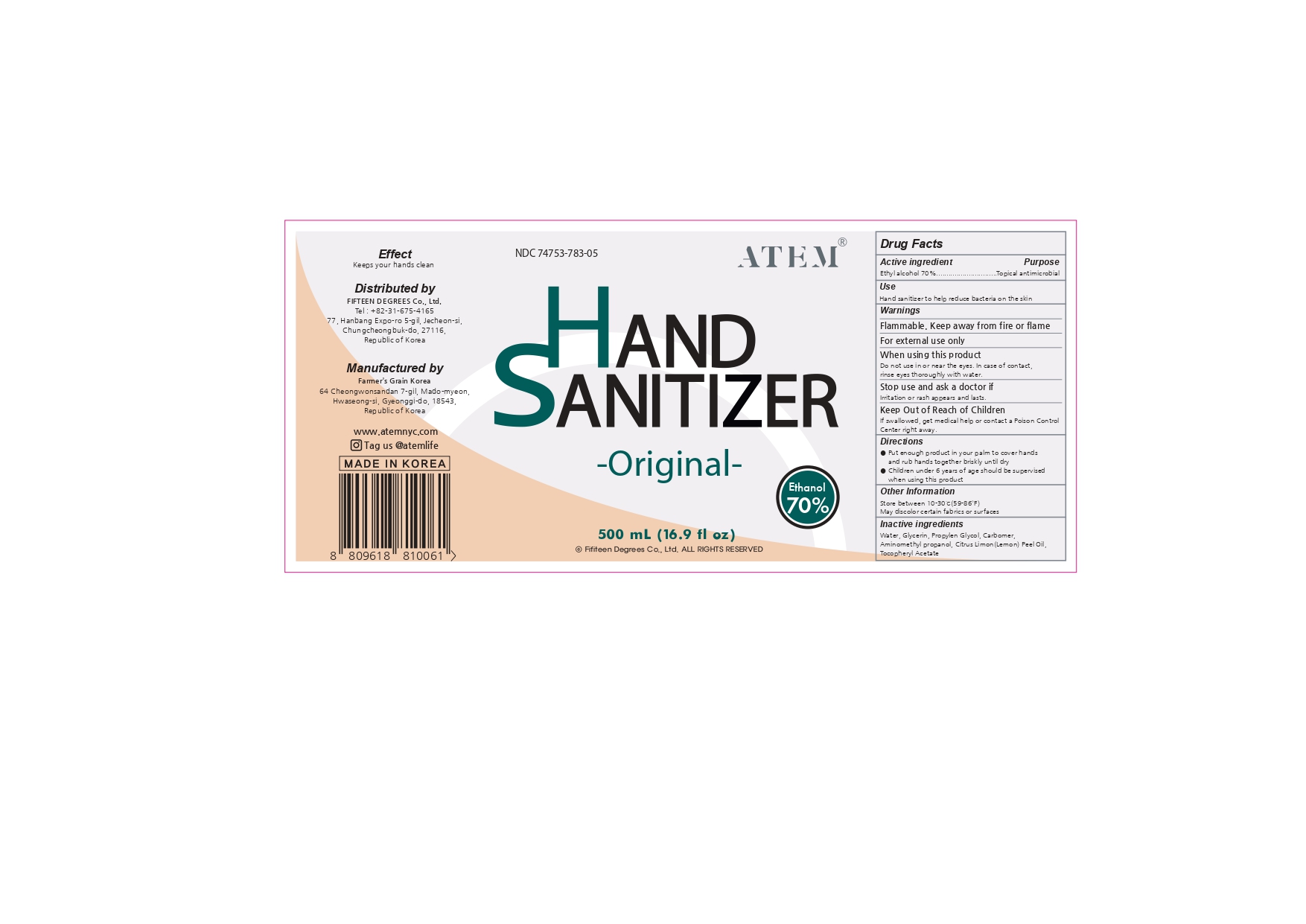 DRUG LABEL: Hand Sanitizer
NDC: 74752-783 | Form: LIQUID
Manufacturer: FARMER'S GRAIN KOREA LTD
Category: otc | Type: HUMAN OTC DRUG LABEL
Date: 20210109

ACTIVE INGREDIENTS: ALCOHOL 70 mL/70 mL
INACTIVE INGREDIENTS: WATER; GLYCERIN; AMINOMETHYLPROPANOL; .ALPHA.-TOCOPHEROL ACETATE, D-; CARBOMER HOMOPOLYMER, UNSPECIFIED TYPE; LEMON OIL; PROPYLENE GLYCOL

Hand Sanitizer farmer grain

ACTIVE INGREDIENT

Ethyl alcohol 70% purpose topical antimicrobial

INACTIVE INGREDIENT

Water

Glycerin

Carbomer

Aminomethyl Propanol

Citrus Limon (Lemon) Peel Oil

Tocopheryl Acetate

Propylene Glycol

WARNINGS

Flammable. Keep away from fire or flame
For external use only
Directions
● Put enough product in your palm to cover hands
● Children under 6years of age should be supervised
Other Information
Inactive ingredients
Drug Facts
When using this product
rinse eyes thoroughly with water.
Stop use and ask a doctor if
irritation or rash appears and lasts
Keep Out of Reach of Children
If swallowed, get medical help or contact a Poison

Directions
● Put enough product in your palm to cover hands
● Children under 6years of age should be supervised

INDICATIONS AND USAGE

Use: Hand sanitizer to help reduce bacteria on the skin

purpose: Topical antimicrobial

Keep Out of Reach of Children
If swallowed, get medical help or contact a Poison Control Center right away.

PACKAGE LABEL

NDC 74753-783-05

atem

hand sanitizer

ethanol 70%

original

500 mL (16.9 fl oz)